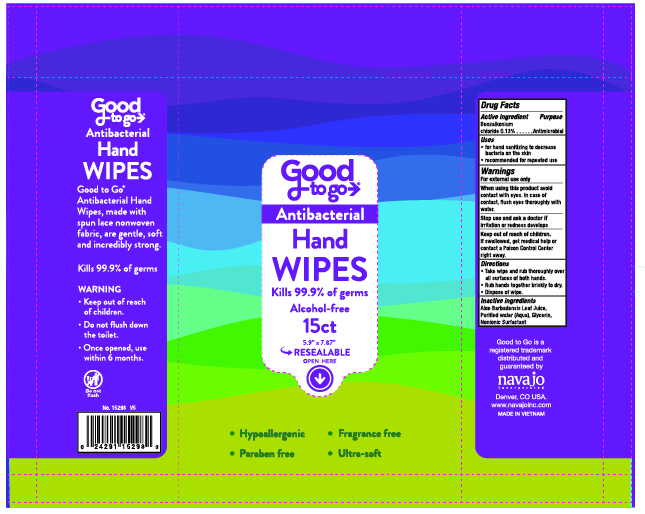 DRUG LABEL: Good to Go Antibacterial Hand Wipes
NDC: 67751-237 | Form: LIQUID
Manufacturer: Navajo Manufacturing Company Inc.
Category: otc | Type: HUMAN OTC DRUG LABEL
Date: 20250717

ACTIVE INGREDIENTS: BENZALKONIUM CHLORIDE 0.13 g/100 g
INACTIVE INGREDIENTS: ALOE; DECYL GLUCOSIDE; WATER; GLYCERIN

Good to Go Antibacterial Hand Wipes 15ct

Active ingredient

Benzalkonium Chloride 0.13%

Purpose

Antimicrobial

Uses

- for hand sanitizing to decrease bacteria on the skin
- recommended for repeated use

Warnings

For external use only.

When using this product avoid contact with eyes. In case of contact, flush eyes thouroughly with water.

Stop use and ask a doctorif irritation or redness develops.

Keep out of reach of children. If swallowed, get medical help or contact a Poison Control Center right away.

Directions

- Take wipe and rub thoroughly over all surfaces of both hands.
- Rub hands together briskly to dry.
- Dispose of wipe.

Inactive ingredients

Aloe Barbadensis Leaf Juice, Purified Water (Aqua), Glycerin, Nonionic Surfactant

Principal Display Panel

Navajo Incorporated

Denver, CO USA

www.navajoinc.com

Made in Vietnam